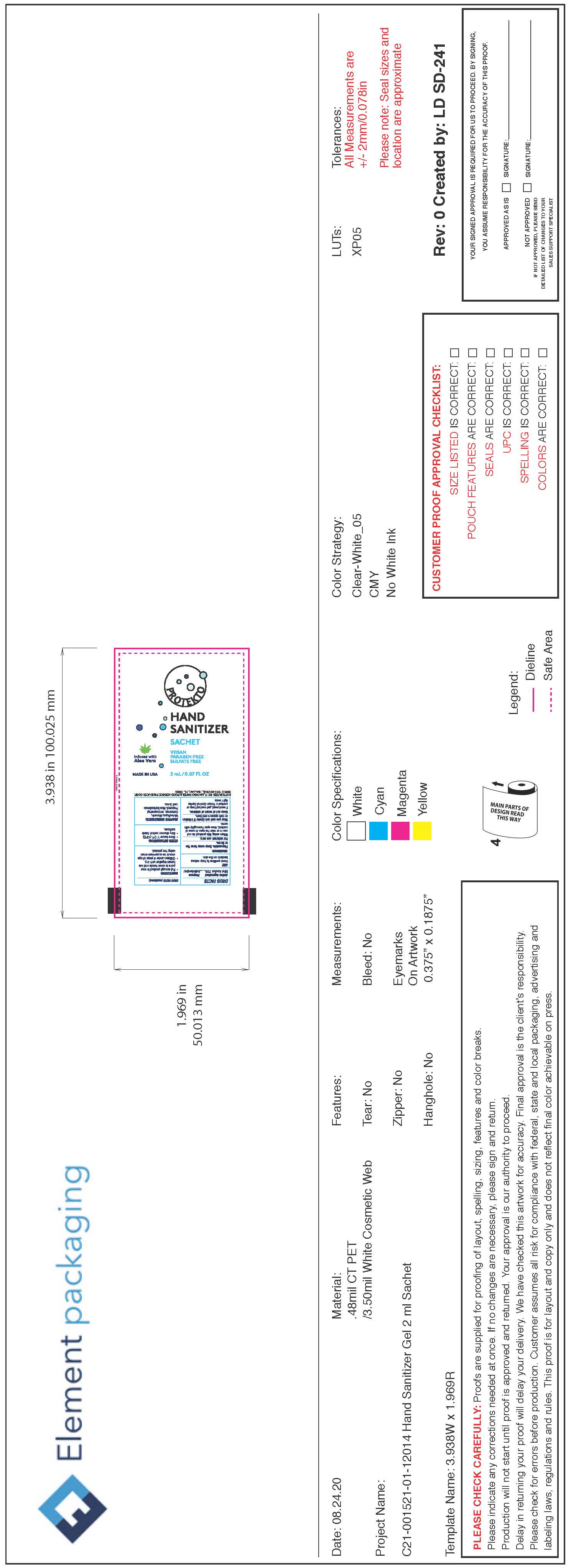 DRUG LABEL: Hand Sanitizer
NDC: 80451-003 | Form: GEL
Manufacturer: Flamingo Paper & Food Services Products, Corp
Category: otc | Type: HUMAN OTC DRUG LABEL
Date: 20200918

ACTIVE INGREDIENTS: ALCOHOL 70.473 mL/100 mL
INACTIVE INGREDIENTS: GLYCERIN 1.496 mL/100 mL; CARBOMER 940 0.5 mL/100 mL; WATER 27.445 mL/100 mL

Protekto Hand Sanitizer Infused with Aloe Vera

Active Ingredient(s)

Alcohol 70%. Purpose: Antimicrobial

Purpose

Antimicrobial, Hand Sanitizer

Use

Hand Sanitizer to help reduce bacteria on the skin.

Warnings

Flammable. Keep away from heat or flame.For external use only.

When using this product do not use in or near the eyes. In case of contact, rinse eyes thoroughly with water.

Stop use and ask a doctor if irritation or rash appears and lasts.

Keep out of reach of children. If swallowed, get medical help or contact a Poison Control Center right away.

Directions

- Put enough product in your palm to cover hands and rub hands together until dry.
- Children under 6 years of age should be supervised when using this product.

Other information

- Store below 110F (43C)
- Avoid freezing and excessive heat above 40C (104F)

Inactive ingredients

Water/Aqua, Glycerin, Carbomer, Aminomethyl Propanol, Aloe Barbadensis Leaf Juice.

Package Label - Principal Display Panel

2mL NDC: 80451-003-01